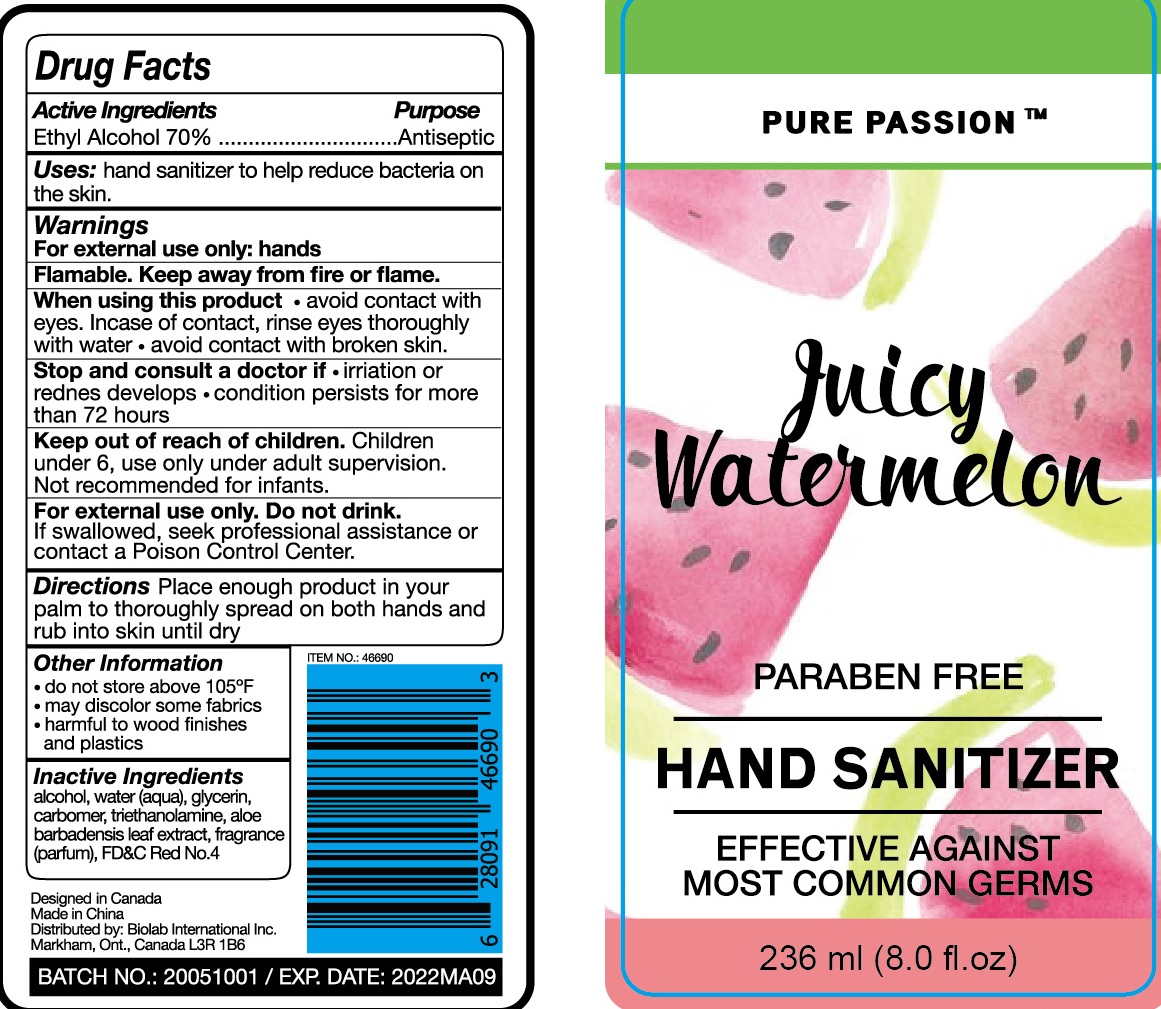 DRUG LABEL: Pure Passion Hand Sanitizer Juicy Watermelon
NDC: 74511-002 | Form: GEL
Manufacturer: Xiamen Meidai Cross-border E-commerce Co., Ltd.
Category: otc | Type: HUMAN OTC DRUG LABEL
Date: 20200504

ACTIVE INGREDIENTS: alcohol 70 mL/100 mL
INACTIVE INGREDIENTS: WATER; PROPYLENE GLYCOL; ALOE VERA LEAF; CARBOMER 934; GLYCERIN; TROLAMINE; FD&C RED NO. 4

Drug facts

Active ingredient(s) Purpose

Ethyl Alcohol 70% ............... Antiseptic

PURPOSE

- Hand sanitizer to help decrease bacteria on the skin.

KEEP OUT OF REACH OF CHILDREN

Children under 6, use only under adult supervision. Not recommended for infants.

if swallowed, seek professional assistance or contact a Poison Control Center.

INDICATIONS AND USAGE

Place enough product in your palm to thoroughly spread on both hands and rub into skin until dry.

WARNINGS

For external use only: hands
Flammable. Keep away from fire or flame.

When using this product, avoid contact with eyes. In case of contact, flush eyes thoroughly with water. Avoid contact with broken skin.

Stop and consult a doctor if irritation or redness develop. Condition persist for more than 72 hours.

Other information:

- Do not store above 105℉
- May discolr some fabrics
- Harmful to wood finishes and plastics.

INACTIVE INGREDIENT

Water (Aqua), Glycerin, carbomer, Triethanolamine, Aloe Barbadensis gel Extract, fragrance (Parfum), FD&C Red No. 4